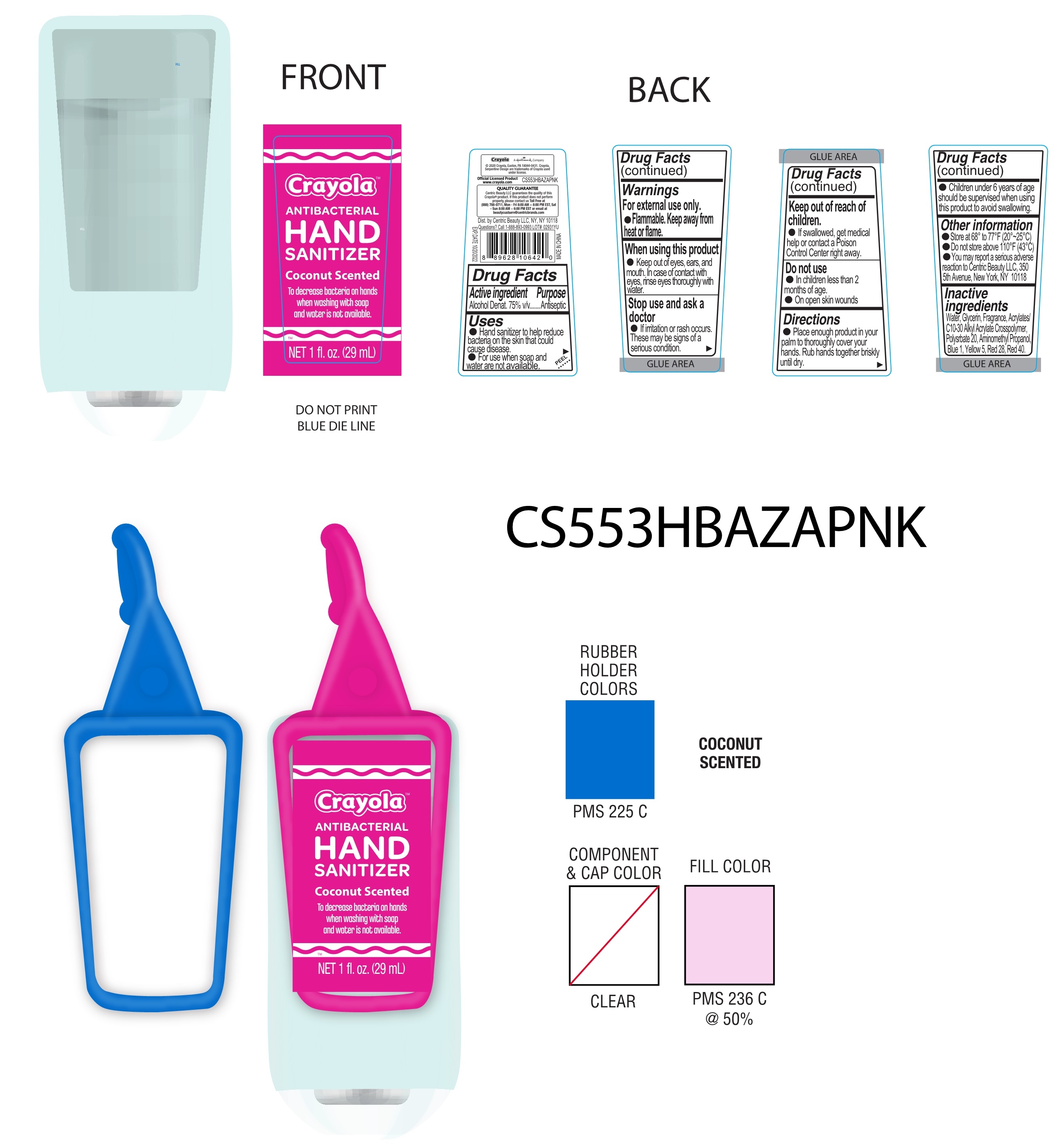 DRUG LABEL: HAND SANITIZER
NDC: 75427-018 | Form: GEL
Manufacturer: Jinhua City Wellmae Cosmetics Co., Ltd.
Category: otc | Type: HUMAN OTC DRUG LABEL
Date: 20220120

ACTIVE INGREDIENTS: ALCOHOL 75 mL/100 mL
INACTIVE INGREDIENTS: POLYSORBATE 20; D&C RED NO. 28; WATER; AMINOMETHYLPROPANOL; GLYCERIN; CARBOMER INTERPOLYMER TYPE A (55000 CPS); FRAGRANCE CLEAN ORC0600327; FD&C BLUE NO. 1; FD&C YELLOW NO. 5; FD&C RED NO. 40

75427-018
粉 HAND SANITIZER

ACTIVE INGREDIENT

Alcohol Denat.75% v/v

Purpose

Antiseptic

Uses

●Hand sanitizer to help reduce bacteria on the skin that could cause disease.
● For use when soap and water are not available.

WARNINGS

For external use only.
●Flammable. Keep away from heat or flame.

When using this poduct
●Keep out of eyes, ears,and mouth, ln case of contact with eyes, rinse eyes thoroughly with water.

Stop use and ask a Doctor
●lf irrition or rash occurs. These may be signs of a serious condition.

Keep out of reach of children.
● lf swallowed, get medical help or contact a Poison Control Center right away.

Do not use
● ln children less than 2 months of age.
● On open skin wounds

Do not use

● ln children less than 2 months of age.
● On open skin wounds

When using this product

When using this poduct
●Keep out of eyes, ears,and mouth, ln case of contact with eyes, rinse eyes thoroughly with water.

Stop use and ask a Doctor
●lf irrition or rash occurs. These may be signs of a serious condition.

Keep out of reach of children.
● lf swallowed, get medical help or contact a Poison Control Center right away.

Do not use
● ln children less than 2 months of age.
● On open skin wounds

Stop use and ask a doctor

●lf irrition or rash occurs. These may be signs of a serious condition.

Keep out of reach of children

● lf swallowed, get medical help or contact a Poison Control Center right away.

Directions

● Place enough product in your palm to thoroughly cover your hands. Rub hands together briskly until dry.
● Children under 6 years of age should be supervised when using this product to avoid swallowing.

Other Information

● Store at 68°to 77℉ (20°~25℃)
● Do not store above 110℉ (43℃)
● You may report a serious adverse reaction to Centric Beauty LLC, 3505th Avenue, New York, NY 10118

Inactive Ingredients

Water, Glycerin, Fragrance, Acrylates/C10-30 Alkyl Acrylate Crosspolymer, Polysrbate 20, Aminomethyl Propanol, Blue 1, Yellow 5, Red 28, Red 40.